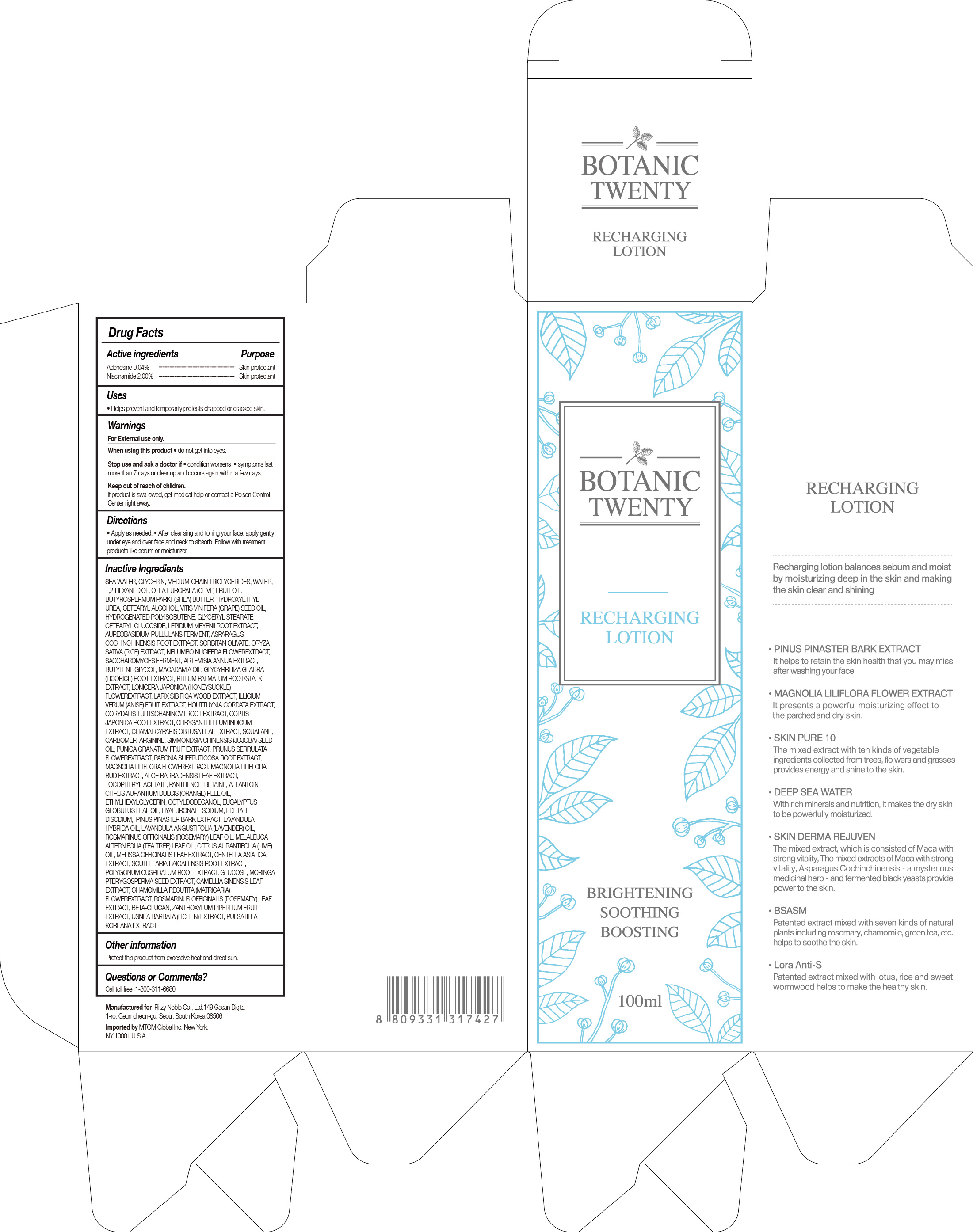 DRUG LABEL: BOTANIC TWENTY
NDC: 71364-002 | Form: LOTION
Manufacturer: RITZY NOBLE CO., LTD.
Category: otc | Type: HUMAN OTC DRUG LABEL
Date: 20180101

ACTIVE INGREDIENTS: ADENOSINE 0.04 g/100 mL; NIACINAMIDE 2 g/100 mL
INACTIVE INGREDIENTS: PINUS PINASTER WOOD; SORBITAN OLIVATE; MELISSA OFFICINALIS LEAF; BETAINE; 1,2-HEXANEDIOL; ARTEMISIA ANNUA WHOLE; SACCHAROMYCES LYSATE; .ALPHA.-TOCOPHEROL ACETATE; HYALURONIC ACID; COPTIS JAPONICA ROOT; CHAMAECYPARIS OBTUSA LEAF; RHEUM PALMATUM ROOT; BUTYLENE GLYCOL; AUREOBASIDIUM PULLULANS VAR. PULLUTANS; WATER; GLYCERIN; LONICERA JAPONICA FLOWER; CORYDALIS TURTSCHANINOVII WHOLE; ILLICIUM VERUM WHOLE; LARIX SIBIRICA WOOD; ETHYLHEXYLGLYCERIN; CITRUS AURANTIUM FRUIT OIL; CENTELLA ASIATICA; EUCALYPTUS GLOBULUS LEAF; POLYGONUM CUSPIDATUM ROOT; SCUTELLARIA BAICALENSIS ROOT; ROSMARINUS OFFICINALIS FLOWERING TOP OIL; ROSMARINUS OFFICINALIS WHOLE; CAMELLIA SINENSIS WHOLE; CHRYSANTHEMUM X MORIFOLIUM FLOWER; MAGNOLIA LILIIFLORA FLOWER; NELUMBO NUCIFERA LEAF; PUNICA GRANATUM SEED; EDETATE DISODIUM; ASPARAGUS COCHINCHINENSIS WHOLE; HYDROXYETHYL UREA; HOUTTUYNIA CORDATA TOP; ORYZA SATIVA WHOLE; ALOE VERA LEAF; GLYCYRRHIZA GLABRA; CARBOMER 934; ARGININE; LAVANDULA ANGUSTIFOLIA WHOLE; MATRICARIA CHAMOMILLA FLOWERING TOP OIL; GLYCERYL MONOSTEARATE; PAEONIA X SUFFRUTICOSA ROOT; VITIS VINIFERA SEED; MEDIUM-CHAIN TRIGLYCERIDES; USNEA BARBATA; ZANTHOXYLUM PIPERITUM WHOLE; MACADAMIA OIL; JOJOBA OIL; PANTHENOL; ANHYDROUS DEXTROSE; MAGNOLIA LILIIFLORA FLOWER BUD; CETOSTEARYL ALCOHOL; LAVANDIN OIL; LEPIDIUM MEYENII ROOT; OLEA EUROPAEA FRUIT VOLATILE OIL; PULSATILLA KOREANA ROOT; MELALEUCA ALTERNIFOLIA LEAF; MORINGA OLEIFERA SEED OIL; OCTYLDODECANOL; PRUNUS SERRULATA FLOWER; SQUALANE; SHEA BUTTER; HYDROGENATED POLYBUTENE (1300 MW); CETEARYL GLUCOSIDE; ALLANTOIN

Botanic Twenty Recharging Lotion

BOTANIC TWENTY RECHARGING LOTION

ACTIVE INGREDIENTS

ADENOSINE 0.04%

NIACINAMIDE 2.00%

PURPOSE

SKIN PROTECTANT

USES

Helps prevent and temporarily protects chapped or cracked skin.

WARNINGS

FOR EXTERNAL USE ONLY

WHEN USING THIS PRODUCT

• do not get into eyes.

STOP USE AND ASK A DOCTOR IF

• condition worsens

• symptoms last more than 7 days or clear up and occurs again within a few days.

KEEP OUT OF REACH OF CHILDREN

If product is swallowed, get medical help or contact a Poison Control Center right away.

DIRECTIONS

• Apply as needed.

• After washing your face, take a suitable amount of the product and softly spread it on your face and neck to be absorbed.

INACTIVE INGREDIENTS

SEA WATER, GLYCERIN, MEDIUM-CHAIN TRIGLYCERIDES, WATER, 1,2-HEXANEDIOL, OLEA EUROPAEA (OLIVE) FRUIT OIL, BUTYROSPERMUM PARKII (SHEA) BUTTER, HYDROXYETHYL UREA, CETEARYL ALCOHOL, VITIS VINIFERA (GRAPE) SEED OIL, HYDROGENATED POLYISOBUTENE, GLYCERYL STEARATE, CETEARYL GLUCOSIDE, LEPIDIUM MEYENII ROOT EXTRACT, AUREOBASIDIUM PULLULANS FERMENT, ASPARAGUS COCHINCHINENSIS ROOT EXTRACT, SORBITAN OLIVATE, ORYZA SATIVA (RICE) EXTRACT, NELUMBO NUCIFERA FLOWEREXTRACT, SACCHAROMYCES FERMENT, ARTEMISIA ANNUA EXTRACT, BUTYLENE GLYCOL, MACADAMIA OIL, GLYCYRRHIZA GLABRA (LICORICE) ROOT EXTRACT, RHEUM PALMATUM ROOT/STALK EXTRACT, LONICERA JAPONICA (HONEYSUCKLE) FLOWEREXTRACT, LARIX SIBIRICA WOOD EXTRACT, ILLICIUM VERUM (ANISE) FRUIT EXTRACT, HOUTTUYNIA CORDATA EXTRACT, CORYDALIS TURTSCHANINOVII ROOT EXTRACT, COPTIS JAPONICA ROOT EXTRACT, CHRYSANTHELLUM INDICUM EXTRACT, CHAMAECYPARIS OBTUSA LEAF EXTRACT, SQUALANE, CARBOMER, ARGININE, SIMMONDSIA CHINENSIS (JOJOBA) SEED OIL, PUNICA GRANATUM FRUIT EXTRACT, PRUNUS SERRULATA FLOWEREXTRACT, PAEONIA SUFFRUTICOSA ROOT EXTRACT, MAGNOLIA LILIFLORA FLOWEREXTRACT, MAGNOLIA LILIFLORA BUD EXTRACT, ALOE BARBADENSIS LEAF EXTRACT, TOCOPHERYL ACETATE, PANTHENOL, BETAINE, ALLANTOIN, CITRUS AURANTIUM DULCIS (ORANGE) PEEL OIL, ETHYLHEXYLGLYCERIN, OCTYLDODECANOL, EUCALYPTUS GLOBULUS LEAF OIL, HYALURONATE SODIUM, EDETATE DISODIUM, PINUS PINASTER BARK EXTRACT, LAVANDULA HYBRIDA OIL, LAVANDULA ANGUSTIFOLIA (LAVENDER) OIL, ROSMARINUS OFFICINALIS (ROSEMARY) LEAF OIL, MELALEUCA ALTERNIFOLIA (TEA TREE) LEAF OIL, CITRUS AURANTIFOLIA (LIME) OIL, MELISSA OFFICINALIS LEAF EXTRACT, CENTELLA ASIATICA EXTRACT, SCUTELLARIA BAICALENSIS ROOT EXTRACT, POLYGONUM CUSPIDATUM ROOT EXTRACT, GLUCOSE, MORINGA PTERYGOSPERMA SEED EXTRACT, CAMELLIA SINENSIS LEAF EXTRACT, CHAMOMILLA RECUTITA (MATRICARIA) FLOWEREXTRACT, ROSMARINUS OFFICINALIS (ROSEMARY) LEAF EXTRACT, BETA-GLUCAN, ZANTHOXYLUM PIPERITUM FRUIT EXTRACT, USNEA BARBATA (LICHEN) EXTRACT, PULSATILLA KOREANA EXTRACT

OTHER INFORMATION

Protect this product from excessive heat and direct sun.

QUESTIONS OR COMMENTS?

Call toll free 1-800-311-6680